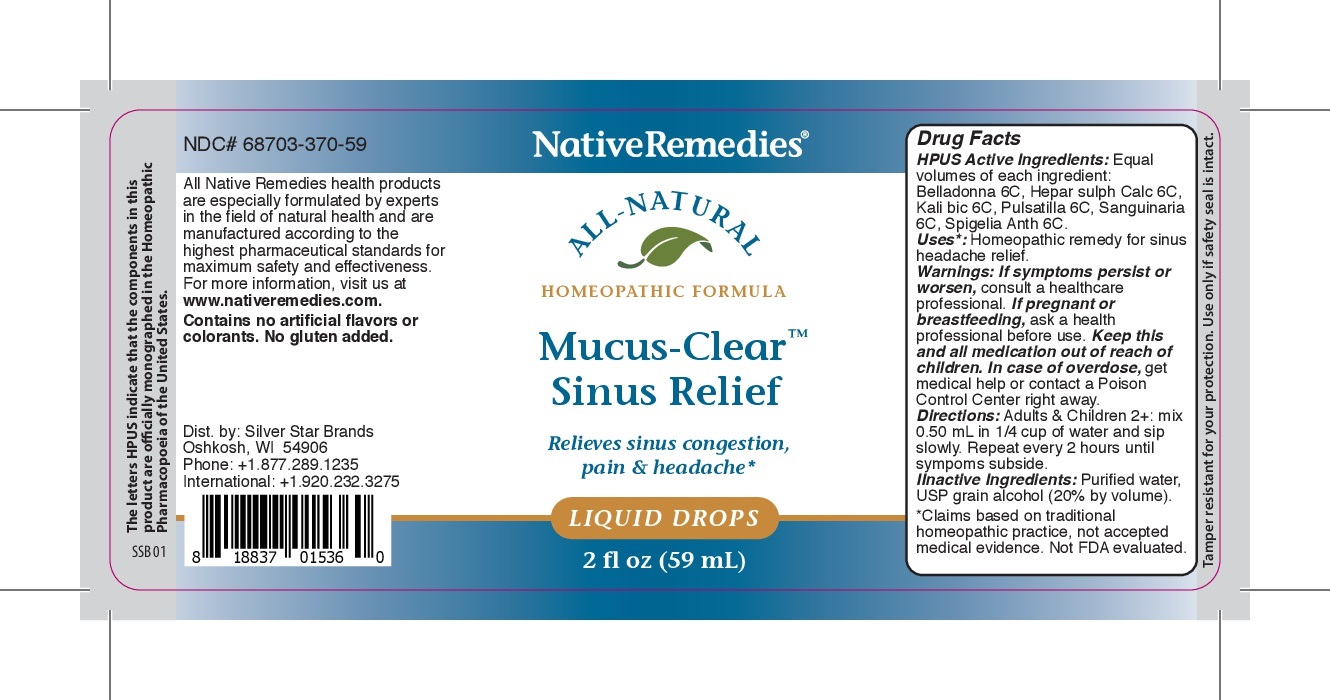 DRUG LABEL: Mucus-Clear Sinus Relief
NDC: 68703-370 | Form: LIQUID
Manufacturer: Silver Star Brands
Category: homeopathic | Type: HUMAN OTC DRUG LABEL
Date: 20250101

ACTIVE INGREDIENTS: ATROPA BELLADONNA 6 [hp_C]/59 mL; SANGUINARIA CANADENSIS ROOT 6 [hp_C]/59 mL; CALCIUM SULFIDE 6 [hp_C]/59 mL; PULSATILLA PATENS WHOLE 6 [hp_C]/59 mL; SPIGELIA ANTHELMIA 6 [hp_C]/59 mL; POTASSIUM DICHROMATE 6 [hp_C]/59 mL
INACTIVE INGREDIENTS: WATER; ALCOHOL

NativeRemedies® Mucus-Clear™ Sinus Relief

HPUS Active Ingredients: Equal volues of each ingredient: Belladonna 6C, Hepar sulph calc 6C, Kali bic 6C, Pulsatilla 6C, Sanguinaria 6C, Spigelia Anth 6C.

Uses*:

Uses*: Homeopathic remedy for sinus headache relief.

*Claims based on traditional homeopathic practice, not accepted medical evidence. Not FDA evaluated.

Warnings:

Warnings: If symptoms persist or worsen, consulta healthcare professional. If pregnant or breastfeeding, ask a health professional before use. Keep this and all medication out of reach of children. In case of overdose, get medical help or contact a Poison Control Center right away.

Directions

Directions: Adults & Children 2+: mix 0.50 mL in 1/4 cup of water and sip slowly. Repeat every 2 hours until symptoms subside.

OTHER SAFETY INFORMATION

Contains no artificial flavors or colorants. No gluten added.

Tamper resistant for your protection. Use only if safety seal is intact.

Inactive Ingredients:

Inactive Ingredients: Purified water, USP grain alcohol (20% by volume).

KEEP OUT OF REACH OF CHILDREN

Keep this and all medication out of reach of children.

PREGNANCY OR BREAST FEEDING

If pregnant or breastfeeding, ask a health professional before use.

PURPOSE

Relieves sinus congestion, pain & headache.